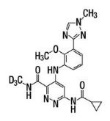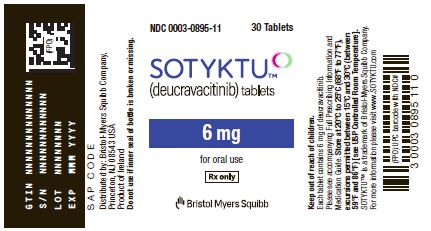 DRUG LABEL: SOTYKTU
NDC: 0003-0895 | Form: TABLET, FILM COATED
Manufacturer: E.R. Squibb & Sons, L.L.C.
Category: prescription | Type: HUMAN PRESCRIPTION DRUG LABEL
Date: 20220909

ACTIVE INGREDIENTS: DEUCRAVACITINIB 6 mg/1 1
INACTIVE INGREDIENTS: ANHYDROUS LACTOSE; CROSCARMELLOSE SODIUM; HYPROMELLOSE ACETATE SUCCINATE 06081224 (3 MM2/S); MAGNESIUM STEARATE; MICROCRYSTALLINE CELLULOSE; SILICON DIOXIDE; POLYVINYL ALCOHOL, UNSPECIFIED; TITANIUM DIOXIDE; POLYETHYLENE GLYCOL, UNSPECIFIED; TALC; FERRIC OXIDE RED; FERRIC OXIDE YELLOW

HIGHLIGHTS OF PRESCRIBING INFORMATION

These highlights do not include all the information needed to use SOTYKTU safely and effectively. See full prescribing information for SOTYKTU.
SOTYKTU™ (deucravacitinib) tablets, for oral use
Initial U.S. Approval: 2022

1 INDICATIONS AND USAGE

SOTYKTU is a tyrosine kinase 2 (TYK2) inhibitor indicated for the treatment of adults with moderate-to-severe plaque psoriasis who are candidates for systemic therapy or phototherapy. (1)
Limitations of Use:
Not recommended for use in combination with other potent immunosuppressants.

2 DOSAGE AND ADMINISTRATION

- For recommended evaluation prior to SOTYKTU initiation, see Full Prescribing Information. (2.1)
- Recommended dosage is 6 mg orally once daily, with or without food. (2.2)

3 DOSAGE FORMS AND STRENGTHS

Tablets: 6 mg (3)

4 CONTRAINDICATIONS

Known hypersensitivity to deucravacitinib or any of the excipients in SOTYKTU. (4, 5.1)

5 WARNINGS AND PRECAUTIONS

- Hypersensitivity: Hypersensitivity reactions such as angioedema have been reported. Discontinue if a clinically significant hypersensitivity reaction occurs. (5.1)
- Infections: SOTYKTU may increase the risk of infection. Avoid use in patients with active or serious infection. If a serious infection develops, discontinue SOTYKTU until the infection resolves. (5.2)
- Tuberculosis: Evaluate for TB prior to initiating treatment with SOTYKTU. (5.3)
- Malignancy: Malignancies including lymphomas were observed in clinical trials with SOTYKTU (5.4)
- Rhabdomyolysis and elevated CPK. (5.5)
- Laboratory Abnormalities: Periodically evaluate serum triglycerides. Evaluate liver enzymes at baseline and thereafter in patients with known or suspected liver disease. (5.6)
- Immunizations: Avoid use with live vaccines. (5.7)
- Potential Risks Related to JAK Inhibition: It is not known whether TYK2 inhibition may be associated with the observed or potential adverse reactions of JAK inhibition. Higher rates of all-cause mortality, including sudden cardiovascular death, major adverse cardiovascular events, overall thrombosis, deep venous thrombosis, pulmonary embolism, and malignancies (excluding non-melanoma skin cancer) were observed in patients treated with a JAK inhibitor compared to those treated with TNF blockers in rheumatoid arthritis (RA) patients. SOTYKTU is not approved for use in RA. (5.8)

6 ADVERSE REACTIONS

Most common adverse reactions (≥ 1%) are upper respiratory infections, blood creatine phosphokinase increased, herpes simplex, mouth ulcers, folliculitis, and acne. (6.1)

To report SUSPECTED ADVERSE REACTIONS, contact Bristol-Myers Squibb at 1-800-721-5072 or FDA at 1-800-FDA-1088 or www.fda.gov/medwatch.

8 USE IN SPECIFIC POPULATIONS

SOTYKTU is not recommended in patients with severe hepatic impairment (Child-Pugh C). (2.3)

FULL PRESCRIBING INFORMATION

1 INDICATIONS AND USAGE

SOTYKTU™ is indicated for the treatment of moderate-to-severe plaque psoriasis in adults who are candidates for systemic therapy or phototherapy.

Limitations of Use:

SOTYKTU is not recommended for use in combination with other potent immunosuppressants.

2 DOSAGE AND ADMINISTRATION

2.1 Recommended Evaluations and Immunizations Prior to Treatment Initiation

Evaluate patients for active and latent tuberculosis (TB) infection prior to initiating treatment with SOTYKTU. If positive, start treatment for TB prior to SOTYKTU use [see Warnings and Precautions (5.3)].

Update immunizations according to current immunization guidelines [see Warnings and Precautions (5.7)].

2.2 Recommended Dosage

The recommended dosage of SOTYKTU is 6 mg taken orally once daily, with or without food.

Do not crush, cut, or chew the tablets.

2.3 Recommended Dosage in Patients with Hepatic Impairment

SOTYKTU is not recommended in patients with severe hepatic impairment (Child-Pugh C) [see Use in Specific Populations (8.7) and Clinical Pharmacology (12.3)].

No dosage adjustment is needed for patients with mild to moderate hepatic impairment.

3 DOSAGE FORMS AND STRENGTHS

Tablets: 6 mg, pink, round, biconvex, laser printed with “BMS 895” and “6 mg” on one side with no content on the other side.

4 CONTRAINDICATIONS

SOTYKTU is contraindicated in patients with a history of hypersensitivity reaction to deucravacitinib or to any of the excipients in SOTYKTU [see Warnings and Precautions (5.1)].

5 WARNINGS AND PRECAUTIONS

5.1 Hypersensitivity

Hypersensitivity reactions such as angioedema have been reported in subjects receiving SOTYKTU. If a clinically significant hypersensitivity reaction occurs, institute appropriate therapy and discontinue SOTYKTU [see Adverse Reactions (6.1)].

5.2 Infections

SOTYKTU may increase the risk of infections.

Serious infections have been reported in subjects with psoriasis who received SOTYKTU. The most common serious infections reported with SOTYKTU included pneumonia and COVID-19 [see Adverse Reactions (6.1)].

Avoid use of SOTYKTU in patients with an active or serious infection.

Consider the risks and benefits of treatment prior to initiating SOTYKTU in patients:

- with chronic or recurrent infection
- who have been exposed to tuberculosis
- with a history of a serious or an opportunistic infection
- with underlying conditions that may predispose them to infection.

Closely monitor patients for the development of signs and symptoms of infection during and after treatment with SOTYKTU. A patient who develops a new infection during treatment with SOTYKTU should undergo prompt and complete diagnostic testing; appropriate antimicrobial therapy should be initiated; and the patient should be closely monitored. Interrupt SOTYKTU if a patient develops a serious infection. Do not resume SOTYKTU until the infection resolves or is adequately treated.

Viral Reactivation

Herpes virus reactivation (e.g., herpes zoster, herpes simplex), was reported in clinical trials with SOTYKTU. In the 16‑week placebo-controlled period, herpes simplex infections were reported in 17 subjects (6.8 per 100 patient‑years) treated with SOTYKTU, and 1 subject (0.8 per 100 patient-years) treated with placebo.

Multidermatomal herpes zoster was reported in an immunocompetent subject who received SOTYKTU.

During PSO-1, PSO-2, and the open-label extension trial in which subjects who completed the controlled trials could enroll, the majority of subjects who reported events of herpes zoster while receiving SOTYKTU were under 50 years of age.

The impact of SOTYKTU on chronic viral hepatitis reactivation is unknown. Subjects with positive screening tests for hepatitis B or C, or chronic hepatitis B, or untreated hepatitis C were excluded from clinical trials. Consider viral hepatitis screening and monitoring for reactivation in accordance with clinical guidelines before starting therapy and during therapy with SOTYKTU. If signs of reactivation occur, consult a hepatitis specialist. SOTYKTU is not recommended for use in patients with active hepatitis B or hepatitis C.

5.3 Tuberculosis

In clinical trials, of 4 subjects with latent tuberculosis (TB) who were treated with SOTYKTU and received appropriate TB prophylaxis, no subjects developed active TB (during the mean follow-up of 34 weeks). One subject, who did not have latent TB, developed active TB after receiving 54 weeks of SOTYKTU.

Evaluate patients for latent and active TB infection prior to initiating treatment with SOTYKTU. Do not administer SOTYKTU to patients with active TB. Initiate treatment of latent TB prior to administering SOTYKTU.

Consider anti-TB therapy prior to initiation of SOTYKTU in patients with a past history of latent or active TB in whom an adequate course of treatment cannot be confirmed. Monitor patients receiving SOTYKTU for signs and symptoms of active TB during treatment.

5.4 Malignancy including Lymphomas

Malignancies, including lymphomas, were observed in clinical trials with SOTYKTU [see Adverse Reactions (6.1)].

Consider the benefits and risks for the individual patient prior to initiating or continuing therapy with SOTYKTU, particularly in patients with a known malignancy (other than a successfully treated non-melanoma skin cancer) and patients who develop a malignancy when on treatment with SOTYKTU.

5.5 Rhabdomyolysis and Elevated CPK

Cases of rhabdomyolysis were reported in subjects treated with SOTYKTU resulting in interruption or discontinuation of SOTYKTU dosing.

Treatment with SOTYKTU was associated with an increased incidence of asymptomatic creatine phosphokinase (CPK) elevation and rhabdomyolysis compared to treatment with placebo. Discontinue SOTYKTU if markedly elevated CPK levels occur or myopathy is diagnosed or suspected. Instruct patients to promptly report any unexplained muscle pain, tenderness or weakness, particularly if accompanied by malaise or fever [see Adverse Reactions (6.1)].

5.6 Laboratory Abnormalities

Triglyceride Elevations - Treatment with SOTYKTU was associated with increases in triglyceride levels. The effect of this elevated parameter on cardiovascular morbidity and mortality has not been determined. Periodically evaluate serum triglycerides according to the clinical guidelines for hyperlipidemia while patients are receiving treatment with SOTYKTU. Manage patients according to clinical guidelines for the management of hyperlipidemia [see Adverse Reactions (6.1)].

Liver Enzyme Elevations - Treatment with SOTYKTU was associated with an increase in the incidence of liver enzyme elevation compared to treatment with placebo. Liver serum transaminase elevations ≥ 3 times the ULN were reported in subjects treated with SOTYKTU. Evaluate liver enzymes at baseline and thereafter in patients with known or suspected liver disease according to routine patient management. If treatment-related increases in liver enzymes occur and drug-induced liver injury is suspected, interrupt SOTYKTU until a diagnosis of liver injury is excluded [see Adverse Reactions (6.1)].

5.7 Immunizations

Prior to initiating therapy with SOTYKTU, consider completion of all age-appropriate immunizations according to current immunization guidelines including prophylactic herpes zoster vaccination. Avoid use of live vaccines in patients treated with SOTYKTU. The response to live or non-live vaccines has not been evaluated.

5.8 Potential Risks Related to JAK Inhibition

It is not known whether TYK2 inhibition may be associated with the observed or potential adverse reactions of Janus Kinase (JAK) inhibition. In a large, randomized, postmarketing safety trial of a JAK inhibitor in rheumatoid arthritis (RA), patients 50 years of age and older with at least one cardiovascular risk factor, higher rates of all-cause mortality, including sudden cardiovascular death, major adverse cardiovascular events, overall thrombosis, deep venous thrombosis, pulmonary embolism, and malignancies (excluding non-melanoma skin cancer) were observed in patients treated with the JAK inhibitor compared to those treated with TNF blockers. SOTYKTU is not approved for use in RA.

6 ADVERSE REACTIONS

The following adverse reactions are discussed in greater detail in other sections of labeling:

- Infections [see Warnings and Precautions (5.2)]
- Malignancy including lymphomas [see Warnings and Precautions (5.4)]
- Laboratory Abnormalities [see Warnings and Precautions (5.6)]

6.1 Clinical Trials Experience

Because clinical trials are conducted under widely varying conditions, adverse reaction rates observed in the clinical trials of a drug cannot be directly compared to rates in the clinical trials of another drug and may not reflect the rates observed in practice.

The safety of SOTYKTU was evaluated in two placebo- and active-controlled trials (PSO-1 and PSO-2) and an open-label extension trial in which subjects who completed PSO-1 or PSO-2 could enroll [see Clinical Studies (14)]. In these clinical trials, a total of 1,519 subjects with moderate-to-severe plaque psoriasis who were candidates for systemic therapy or phototherapy received SOTYKTU 6 mg orally once daily. Of these, 1,141 subjects were exposed to SOTYKTU for at least one year.

In trials PSO-1 and PSO-2, 1,681 subjects were randomized to receive SOTYKTU 6 mg (840 subjects), placebo (419 subjects), or apremilast 30 mg twice daily (422 subjects). All subjects randomized to placebo switched to SOTYKTU at Week 16. All other subjects remained in their original treatment group until Week 24, at which point subjects could have continued on the same treatment or be switched to SOTYKTU or placebo. The mean age of subjects was 47 years. The majority of subjects were White (87%) and male (67%).

In the 16-week placebo-controlled period of the pooled clinical trials (PSO-1 and PSO-2), discontinuation of therapy due to adverse reactions in subjects who received SOTYKTU was 2.4%, compared to 3.8% for placebo.

Table 1 summarizes the adverse reactions that occurred in at least 1% of subjects in the SOTYKTU group and at a higher rate than the placebo group during the 16-week controlled period.

Table 1: Adverse Reactions that Occurred in ≥ 1% of Subjects with Plaque Psoriasis in the SOTYKTU Group and More Frequently than in the Placebo Group in Trials PSO-1 and PSO-2 through Week 16
Adverse Reaction | SOTYKTU 6 mg once daily | Placebo
 | N=840 n (%) | N=419 n (%)
Upper respiratory infectionsa | 161 (19.2) | 62 (14.8)
Blood creatine phosphokinase increased | 23 (2.7) | 5 (1.2)
Herpes simplexb | 17 (2.0) | 1 (0.2)
Mouth ulcersc | 16 (1.9) | 0 (0.0)
Folliculitis | 14 (1.7) | 0 (0.0)
Acned | 12 (1.4) | 1 (0.2)
a Includes upper respiratory tract infection (viral, bacterial, and unspecified), nasopharyngitis, pharyngitis (including viral, streptococcal, and unspecified), sinusitis (includes acute, viral, bacterial), rhinitis, rhinotracheitis, tracheitis, laryngitis, and tonsillitis (including bacterial, streptococcal)
b Includes oral herpes, genital herpes, herpes simplex, and herpes virus infection
c Includes mouth ulceration, aphthous ulcer, tongue ulceration, and stomatitis
d Includes acne, acne cystic, and dermatitis acneiform

Adverse reactions that occurred in < 1% of subjects in the SOTYKTU group were herpes zoster.

Specific Adverse Reactions

Exposure adjusted incidence rates are reported for all the adverse reactions presented below.

Infections

In the 16-week placebo-controlled period, infections occurred in 29% of the SOTYKTU group (116 events per 100 person-years) compared to 22% of the placebo group (83.7 events per 100 person-years). The majority of infections were non-serious and mild to moderate in severity and did not lead to discontinuation of SOTYKTU.

In the 16-week placebo-controlled period, serious infections were reported in 5 subjects (2.0 per 100 patient-years) treated with SOTYKTU, and 2 subjects (1.6 per 100 patient-years) treated with placebo.

The most common serious infections reported during the 52-week treatment period were pneumonia and COVID-19.

Malignancies

During the 0-to-52-week treatment period of the two clinical trials, PSO-1 and PSO-2 (total exposure of 986 patient-years with SOTYKTU), malignancies (excluding non-melanoma skin cancer) were reported in 3 subjects treated with SOTYKTU (0.3 per 100 patient-years), including single cases each of breast cancer, hepatocellular carcinoma, and lymphoma after 24, 32, and 25 weeks of treatment, respectively.

During PSO-1, PSO-2, and the open-label extension trial in which subjects who completed the controlled trials could enroll, a total of 3 subjects (0.1 per 100 patient-years), developed lymphoma while receiving SOTYKTU after 25, 77, and 98 weeks of treatment.

Laboratory Abnormalities

Creatine Phosphokinase (CPK)

In the 16-week placebo-controlled period, increased CPK (including Grade 4) was reported in 23 subjects (9.3 per 100 patient-years) treated with SOTYKTU, and 5 subjects (4.1 per 100 patient-years) treated with placebo.

Liver Enzyme Elevations

Events of increases in liver enzymes ≥3 times the ULN were observed in subjects treated with SOTYKTU [see Warnings and Precautions (5.5)]. In the 16-week placebo-controlled period:

- ALT elevations ≥3 times the ULN was reported in 9 subjects (3.6 per 100 patient- years) treated with SOTYKTU, and 2 subjects (1.6 per 100 patient-years) treated with placebo.
- AST elevations ≥3 times the ULN was reported in 13 subjects (5.2 per 100 patient- years) treated with SOTYKTU, and 2 subjects (1.6 per 100 patient-years) treated with placebo.

Decreased Glomerular Filtration Rate (GFR)

In the 16-week placebo-controlled period in subjects who had moderate renal impairment (eGFR 30-59 mL/min) at baseline, decreased GFR was reported in 4 subjects (1.6 per 100 patient-years) treated with SOTYKTU, and 1 subject (0.8 per 100 patient-years) treated with placebo. Two of the deucravacitinib-treated subjects had worsening of baseline proteinuria.

Lipid Elevations

Mean triglycerides increased by 10.3 mg/dL during the 16-week treatment period in subjects treated with SOTYKTU and by 9.1 mg/dL during the 52-week treatment period.

Safety Through Week 52

In PSO-1 and PSO-2, the exposure adjusted incidence rate of adverse reactions in subjects treated with SOTYKTU from Week 0 through Week 52 without switching treatment did not increase compared to the rate observed during the first 16 weeks of treatment.

8 USE IN SPECIFIC POPULATIONS

8.1 Pregnancy

Risk Summary

Available data from case reports on SOTYKTU use during pregnancy are insufficient to evaluate a drug-associated risk of major birth defects, miscarriage, or adverse maternal or fetal outcomes.

In animal reproduction studies, no effects on embryo-fetal development were observed with oral administration of deucravacitinib to rats and rabbits during organogenesis at doses that were at least 91 times the maximum recommended human dose (MRHD) of 6 mg once daily (see Data).

All pregnancies have a background risk of birth defect, loss, or other adverse outcomes. The background risk of major birth defects and miscarriage for the indicated population is unknown. In the U.S. general population, the estimated background risk of major birth defects and miscarriage in clinically recognized pregnancies is 2% to 4% and 15% to 20%, respectively.

Report pregnancies to the Bristol-Myers Squibb Company’s Adverse Event reporting line at 1-800-721-5072.

Data

Animal data

Deucravacitinib was administered orally during the period of organogenesis at doses of 5, 15, or 75 mg/kg/day in rats and 1, 3, or 10 mg/kg/day in rabbits. Deucravacitinib was not associated with embryo-fetal lethality or fetal malformations in either species. These doses resulted in maternal exposures (AUC) that were 266 times (rat) or 91 times (rabbit) the exposure at the MRHD.

In a pre- and post-natal development study in rats, deucravacitinib was administered orally from gestation day 6 through lactation day 20, at doses of 5, 15, or 50 mg/kg/day. At 50 mg/kg/day, F1 offspring had reduced body weight gains during the pre-weaning period. After weaning, body weights of affected F1 offspring gradually normalized to control levels. No maternal effects were observed at 50 mg/kg/day (110 times the MRHD based on AUC comparison). No deucravacitinib-related effects on postnatal developmental, neurobehavioral, or reproductive performance of offspring were noted at doses up to 15 mg/kg/day (19 times the MRHD based on AUC comparison).

8.2 Lactation

Risk Summary

There are no data on the presence of deucravacitinib in human milk, the effects on the breastfed infant, or the effects on milk production. Deucravacitinib is present in rat milk. When a drug is present in animal milk, it is likely that the drug will be present in human milk (see Data). The developmental and health benefits of breastfeeding should be considered along with the mother’s clinical need for SOTYKTU and any potential adverse effects on the breastfed infant from SOTYKTU or from the underlying maternal condition.

Data

Animal Data

A single oral dose of 5 mg/kg radiolabeled deucravacitinib was administered to lactating (post-partum days 8 to 12) rats. Deucravacitinib and/or its metabolites were present in the milk of lactating rats.

8.4 Pediatric Use

The safety and effectiveness of SOTYKTU in pediatric patients have not been established.

8.5 Geriatric Use

Of the 1,519 subjects with plaque psoriasis treated with SOTYKTU, 152 (10%) subjects were 65 years or older and 21 (1.4%) subjects were 75 years or older.

During the Week 0-16 period, for those subjects (80 subjects ≥ 65 years old, including 12 subjects ≥ 75 years old) who received SOTYKTU without switching treatment arms, there was a higher rate of overall serious adverse reactions, including serious infections, and discontinuations due to adverse reactions compared with younger adults.

No overall differences in effectiveness of SOTYKTU have been observed between patients 65 years of age and older and younger adult patients.

8.6 Renal Impairment

No dose adjustment of SOTYKTU is recommended in patients with mild, moderate, or severe renal impairment or in patients with end stage renal disease (ESRD) on dialysis [see Clinical Pharmacology (12.3)].

8.7 Hepatic Impairment

No dose adjustment of SOTYKTU is recommended in patients with mild (Child-Pugh A) or moderate (Child-Pugh B) hepatic impairment. SOTYKTU is not recommended for use in patients with severe hepatic impairment (Child-Pugh C) [see Adverse Reactions (6.1) and Clinical Pharmacology (12.3)].

10 OVERDOSAGE

There is no experience regarding human overdosage with SOTYKTU. In case of overdose, consider contacting the Poison Help line (1-800-222-1222) for additional overdosage management recommendations.

The extent of deucravacitinib elimination by hemodialysis was small (5.4% of dose per dialysis treatment), and thus hemodialysis for treatment of overdose with SOTYKTU is limited.

11 DESCRIPTION

Deucravacitinib is a tyrosine kinase 2 (TYK2) inhibitor and is described chemically as:

6-(cyclopropanecarbonylamido)-4-[2-methoxy-3-(1-methyl-1,2,4-triazol-3-yl)anilino]-N-(trideuteriomethyl)pyridazine-3-carboxamide.

The molecular formula is C20H19D3N8O3 and the molecular weight of the free base is 425.47. Deucravacitinib has the structural formula:

Deucravacitinib is a white to yellow powder. The solubility of deucravacitinib is pH dependent. Solubility decreases with increasing pH.

SOTYKTU (deucravacitinib) tablets are supplied in 6 mg strength for oral administration. Each tablet contains deucravacitinib as the active ingredient and the following inactive ingredients: anhydrous lactose, croscarmellose sodium, hypromellose acetate succinate, magnesium stearate, microcrystalline cellulose, and silicon dioxide. In addition, the film coating Opadry® II Pink contains the following inactive ingredients: iron oxide red, iron oxide yellow, polyethylene glycol, polyvinyl alcohol, talc, and titanium dioxide.

12 CLINICAL PHARMACOLOGY

12.1 Mechanism of Action

Deucravacitinib is an inhibitor of tyrosine kinase 2 (TYK2). TYK2 is a member of the Janus kinase (JAK) family. Deucravacitinib binds to the regulatory domain of TYK2, stabilizing an inhibitory interaction between the regulatory and the catalytic domains of the enzyme. This results in allosteric inhibition of receptor-mediated activation of TYK2 and its downstream activation of Signal Transducers and Activators of Transcription (STATs) as shown in cell-based assays. JAK kinases, including TYK2, function as pairs of homo- or heterodimers in the JAK-STAT pathways. TYK2 pairs with JAK1 to mediate multiple cytokine pathways and also pairs with JAK2 to transmit signals as shown in cell-based assays. The precise mechanism linking inhibition of TYK2 enzyme to therapeutic effectiveness in the treatment of adults with moderate-to-severe plaque psoriasis is not currently known.

12.2 Pharmacodynamics

In patients with psoriasis, deucravacitinib reduced psoriasis-associated gene expression in psoriatic skin in a dose dependent manner, including reductions in IL-23-pathway and type I IFN pathway regulated genes. Deucravacitinib reduced IL-17A, IL-19 and beta-defensin by 47 to 50%, 72%, and 81 to 84% respectively following 16 weeks of once daily treatment. The relationship between these pharmacodynamic markers and the mechanism(s) by which deucravacitinib exerts its clinical effects is unknown.

Cardiac Electrophysiology

At a dose 6 times the recommended dose of the 6 mg once daily in psoriasis patients, SOTYKTU does not prolong the QTc interval to any clinically relevant extent.

12.3 Pharmacokinetics

Following oral administration, deucravacitinib plasma Cmax and AUC increased proportionally over a dose range from 3 mg to 36 mg (0.5 to 6 times the approved recommended dosage) in healthy subjects. The accumulation of deucravacitinib was <1.4-fold following once daily dosing in healthy subjects. The PK of deucravacitinib and its active metabolite, BMT‑153261, were comparable between healthy subjects and subjects with psoriasis. The steady state Cmax and AUC24 of deucravacitinib following administration of 6 mg once daily were 45 ng/mL and 473 ng·hr/mL, respectively. The steady state Cmax and AUC24 of the active deucravacitinib metabolite, BMT-153261, following administration of 6 mg once daily were 5 ng/mL and 95 ng·hr/mL, respectively.

Absorption

The absolute oral bioavailability of deucravacitinib was 99% and the median Tmax ranged from 2 to 3 hours in healthy subjects.

Food Effect

No clinically significant differences in the pharmacokinetics of deucravacitinib were observed following administration of a high-fat, high-calorie meal (951 kcal in total, with approximate distribution of 52% fat, 33% carbohydrate and 15% protein). Cmax and AUC of deucravacitinib when administered with food were decreased by approximately 24% and 11%, respectively, and Tmax was prolonged by 1 hour. Cmax and AUC of BMT-153261 when administered with food were decreased by approximately 23% and 10%, respectively, and Tmax was prolonged by 2 hours.

Distribution

The volume of distribution of deucravacitinib at steady state is 140 L. Protein binding of deucravacitinib was 82 to 90% and the blood-to-plasma concentration ratio was 1.26.

Elimination

The terminal half-life of deucravacitinib was 10 hours. The renal clearance of deucravacitinib ranged from 27 to 54 mL/minute.

Metabolism

Deucravacitinib is metabolized by cytochrome P-450 (CYP) 1A2 to form major metabolite BMT-153261. Deucravacitinib is also metabolized by CYP2B6, CYP2D6, carboxylesterase (CES) 2, and uridine glucuronyl transferase (UGT) 1A9.

The active deucravacitinib metabolite, BMT-153261, has comparable potency to the parent drug, but the circulating exposure of BMT-153261 accounts for approximately 20% of the systemic exposure of the total drug-related components.

Excretion

After a single dose of radiolabeled deucravacitinib, approximately 13% and 26% of the dose was recovered as unchanged in urine and feces, respectively. Approximately 6% and 12% of the dose was detected as BMT-153261 in urine and feces, respectively.

Specific Populations

Patients with Renal Impairment

Deucravacitinib Cmax was 14% lower and 6% higher in patients with mild (eGFR ≥60 to <90 mL/min/1.73m^2) and moderate (eGFR ≥30 to <60 mL/min/1.73m^2) renal impairment, compared to subjects with normal renal function (eGFR ≥ 90 mL/min/1.73m^2); no change in Cmax was observed in patients with severe (eGFR <30 mL/min/1.73m^2) renal impairment, and ESRD (eGFR <15 mL/min/1.73m^2) on dialysis. Deucravacitinib AUCinf was unchanged in patients with mild renal impairment but higher by 39%, 28% and 34% in patients with moderate, severe and ESRD on dialysis, respectively, compared to subjects with normal renal function.

BMT-153261 Cmax was 11% lower, 8% lower, 28% higher and 9% higher in patients with mild, moderate, severe renal impairment and ESRD on dialysis, respectively, compared to subjects with normal renal function. BMT-153261 AUCinf was 2% lower, 24% higher, 81% higher and 27% higher in patients with mild, moderate, severe renal impairment and ESRD on dialysis, respectively, compared to subjects with normal renal function.

Dialysis did not substantially clear deucravacitinib from systemic circulation (5.4% of dose cleared per dialysis).

Patients with Hepatic Impairment

Deucravacitinib Cmax was higher by 4%, 10% and 1% in patients with mild (Child-Pugh Class A), moderate (Child-Pugh Class B), and severe (Child-Pugh Class C) hepatic impairment, respectively, compared to subjects with normal hepatic function. Deucravacitinib AUCinf was higher by 10%, 40% and 43% in patients with mild, moderate, and severe hepatic impairment, respectively, compared to subjects with normal hepatic function.

BMT-153261 Cmax was lower by 25%, 59% and 79% in patients with mild, moderate, and severe hepatic impairment, respectively, compared to subjects with normal hepatic function. BMT-153261 AUCinf was lower by 3%, 20% and 50% in patients with mild, moderate, and severe hepatic impairment, respectively, compared to subjects with normal hepatic function [see Use in Specific Populations (8.7)].

Body weight, gender, race, and age did not have a clinically meaningful effect on deucravacitinib exposure.

Drug Interaction Studies

Clinical Trials

No clinically significant differences in the pharmacokinetics of deucravacitinib were observed when co-administered with the following drugs: Cyclosporine (dual Pgp/BCRP inhibitor), fluvoxamine (CYP1A2 inhibitor), ritonavir (CYP1A2 inducer), diflunisal (UGT 1A9 inhibitor), pyrimethamine (OCT1 inhibitor), famotidine (H2 receptor antagonist), or rabeprazole (proton pump inhibitor).

No clinically significant differences in the pharmacokinetics of the following drugs were observed when co-administered with deucravacitinib: Rosuvastatin, methotrexate, mycophenolate mofetil (MMF) and oral contraceptives (norethindrone acetate and ethinyl estradiol).

In Vitro Studies

Cytochrome P450 (CYP) Enzymes: Deucravacitinib is not an inhibitor of CYP1A2, CYP2B6, CYP2C8, CYP2C9, CYP2C19, CYP2D6, or CYP3A4. Deucravacitinib is not an inducer of CYP1A2, CYP2B6, or CYP3A4.

Carboxylesterase (CES) Enzymes: Deucravacitinib is not an inhibitor of CES2.

Uridine diphosphate (UDP)-glucuronosyl transferase (UGT) Enzymes: Deucravacitinib is not an inhibitor of UGT1A1, UGT1A4, UGT1A6, UGT1A9, or UGT2B7.

Transporter Systems: Deucravacitinib is a substrate of Pgp, BCRP, and OCT1, but not OATP, NTCP, OAT1, OAT3, OCT2, MATE1, or MATE2K. Deucravacitinib is an inhibitor of BCRP and OATP1B3, but not an inhibitor of Pgp, OATP1B1, NTCP, BSEP, MRP2, OAT1, OAT3, OCT1, OCT2, MATE1, or MATE2-K.

13 NONCLINICAL TOXICOLOGY

13.1 Carcinogenesis, Mutagenesis, Impairment of Fertility

The carcinogenic potential of deucravacitinib was assessed in 2-year rat and 6-month rasH2 transgenic mouse studies. No evidence of tumorigenicity was observed in male or female rats that received deucravacitinib at oral doses up to 15 mg/kg/day (51 times the MRHD based on AUC comparison). No evidence of tumorigenicity was observed in male or female Tg.rasH2 mice that received deucravacitinib at oral doses up to 60 mg/kg/day.

Deucravacitinib was not mutagenic in a bacterial mutagenicity assay (Ames test) or clastogenic in an in vitro chromosomal aberration assay (cultured Chinese hamster ovary cells) or in an in vivo rat peripheral blood micronucleus assay.

In male rats, deucravacitinib had no effects on reproductive parameters (mating, fertility, and sperm morphology) or early embryonic development of their offspring at oral doses up to 50 mg/kg/day (224 times the MRHD based on AUC comparison).

In female rats, deucravacitinib had no effects on mating, fertility, or early embryonic parameters at oral doses up to 50 mg/kg/day (171 times the MRHD based on AUC comparison).

14 CLINICAL STUDIES

14.1 Plaque Psoriasis

The efficacy and safety of SOTYKTU 6 mg once daily were assessed in two multicenter, randomized, double-blind, placebo- and active-controlled clinical trials, PSO-1 (NCT03624127) and PSO-2 (NCT03611751) which enrolled subjects 18 years of age and older with moderate-to-severe plaque psoriasis who were eligible for systemic therapy or phototherapy. Subjects had a body surface area (BSA) involvement of ≥ 10%, a Psoriasis Area and Severity Index (PASI) score ≥ 12, and a static Physician’s Global Assessment (sPGA) ≥ 3 (moderate or severe).

In PSO-1 and PSO-2, efficacy was assessed in 1,684 subjects randomized to either SOTYKTU (6 mg orally once daily), placebo, or apremilast (30 mg orally twice daily).

Endpoints

Both trials assessed the responses at Week 16 compared to placebo for the two co-primary endpoints:

- proportion of subjects who achieved a sPGA score of 0 (clear) or 1 (almost clear) with at least a 2-grade improvement from baseline;
- the proportion of subjects who achieved at least a 75% improvement in PASI scores from baseline (PASI 75).

Other comparisons between SOTYKTU and placebo that were secondary endpoints at Week 16:

- the proportion of subjects who achieved PASI 90, PASI 100, sPGA 0, scalp severity PGA (ss-PGA) score of 0 (clear) or 1 (almost clear) with at least 2-grade improvement, and Psoriasis Symptoms and Signs Diary (PSSD) Symptom Score of 0 (symptom-free).

Comparisons between SOTYKTU and apremilast were made for the following secondary endpoints at these time points:

- at Week 16 and Week 24 (PSO-1 and PSO-2), the proportion of subjects who achieved PASI 75, PASI 90, and sPGA 0/1 with at least a 2-grade improvement from baseline
- at Week 16 (PSO-1 and PSO-2), the proportion of subjects who achieved sPGA 0 and ss-PGA 0/1 with at least a 2-grade improvement from baseline (scalp).

Results

In both trials, the mean age was 47 years, the mean weight was 91 kg, 67% of subjects were male, 13% were Hispanic or Latino, 87% were White, 2% were Black, and 10% were Asian. At baseline, subjects had a median affected BSA of 20% and a median PASI score of 19. The proportion of subjects with sPGA score of 3 (moderate) and 4 (severe) at baseline were 80% and 20%, respectively. Approximately 18% of subjects had a history of psoriatic arthritis.

Across both trials, 40% of subjects had received prior phototherapy, 42% were naive to any systemic therapy (including biologic and/or non-biologic treatment), 41% received prior non-biologic systemic treatment, and 35% had received prior biologic therapy.

Table 2 presents the efficacy results of SOTYKTU compared to apremilast and placebo in PSO-1. Table 3 presents the efficacy results in PSO-2.

Table 2: Efficacy Results in Adults with Moderate to Severe Plaque Psoriasis (NRIa) in PSO-1
Endpoint | SOTYKTU; (N=330); n (%) | Placebo; (N=166); n (%) | Apremilast; (N=168); n (%) | Difference, % (95% CI)b
Endpoint | SOTYKTU; (N=330); n (%) | Placebo; (N=166); n (%) | Apremilast; (N=168); n (%) | Difference from Placebo | Difference from Apremilast
sPGA response of 0/1 (clear or almost clear)
Week 16c | 178 (54) | 12 (7) | 54 (32) | 47 (40, 53) | 22 (13, 30)
Week 24 | 194 (59) | - | 52 (31) | - | 27 (19, 36)
sPGA response of 0
Week 16 | 58 (18) | 1 (1) | 8 (5) | 17 (13, 21) | 13 (8, 18)
PASI 75 response
Week 16c | 193 (58) | 21 (13) | 59 (35) | 46 (39, 53) | 23 (14, 32)
Week 24 | 228(69) | - | 64 (38) | - | 31 (22, 40)
PASI 90 response
Week 16 | 118 (36) | 7 (4) | 33 (20) | 32 (26, 38) | 16 (8, 24)
Week 24 | 140 (42) | - | 37 (22) | - | 20 (12, 28)
PASI 100 response
Week 16 | 47 (14) | 1 (1) | - | 14 (10, 18) | -
ss-PGA response of 0/1 (scalp)d | (N=209) | (N=121) | (N=110)
Week 16 | 147 (70) | 21 (17) | 43 (39) | 53 (44, 62) | 30 (19, 41)
CI = Confidence interval; PASI = Psoriasis Area and Severity Index; sPGA = Static Physician Global Assessment; ss-PGA = Scalp Specific Physician’s Global Assessment
a NRI = Non-Responder Imputation
b Adjusted difference in proportions is the weighted average of the treatment differences across region, body weight and prior biologic use with the Cochran-Mantel-Haenszel weights.
c Co-primary endpoints comparing SOTYKTU to placebo
d Includes only subjects with baseline ss-PGA score of ≥ 3

Table 3: Efficacy Results in Adults with Moderate to Severe Plaque Psoriasis (NRIa) in PSO-2
Endpoint | SOTYKTU; (N=511); n (%) | Placebo; (N=255); n (%) | Apremilast; (N=254); n (%) | Difference, % (95% CI)b
Endpoint | SOTYKTU; (N=511); n (%) | Placebo; (N=255); n (%) | Apremilast; (N=254); n (%) | Difference from Placebo | Difference from Apremilast
sPGA response of 0/1 (clear or almost clear)
Week 16c | 253 (50) | 22 (9) | 86 (34) | 41 (35, 46) | 16 (9, 23)
Week 24 | 251 (49) | - | 75 (30) | - | 20 (13, 27)
sPGA response of 0
Week 16 | 80 (16) | 3 (1) | 16 (6) | 14 (11, 18) | 9 (5, 14)
PASI 75 response
Week 16c | 271 (53) | 24 (9) | 101 (40) | 44 (38, 49) | 13 (6, 21)
Week 24 | 296 (58) | - | 96 (38) | - | 20 (13, 27)
PASI 90 response
Week 16 | 138 (27) | 7 (3) | 46 (18) | 24 (20, 29) | 9 (3, 15)
Week 24 | 164 (32) | - | 50 (20) | - | 13 (6, 19)
PASI 100 response
Week 16 | 52 (10%) | 3 (1) | - | 9 (6, 12) | -
ss-PGA response of 0/1 (scalp)d | (N=305) | (N=173) | (N=166)
Week 16 | 182 (60) | 30 (17) | 61 (37) | 42 (34, 50) | 23 (14, 33)
CI = Confidence interval; PASI = Psoriasis Area and Severity Index; sPGA = Static Physician Global Assessment; ss-PGA = Scalp Specific Physician’s Global Assessment
a NRI = Non-Responder Imputation
b Adjusted difference in proportions is the weighted average of the treatment differences across region, body weight and prior biologic use with the Cochran-Mantel-Haenszel weights.
c Co-primary endpoints comparing SOTYKTU to placebo
d Includes only subjects with baseline ss-PGA score of ≥ 3

Examination of age, gender, race, body weight, baseline disease severity, and prior systemic therapy did not identify differences in response to SOTYKTU at Week 16 among these subgroups.

Maintenance and Durability of Response

In PSO-1, among subjects who received SOTYKTU and had sPGA 0/1 response at Week 24, the sPGA 0/1 response at Week 52 was 78% (151/194). Among subjects who received SOTYKTU and had PASI 75 response at Week 24, the PASI 75 response at Week 52 was 82% (187/228). Among subjects who received SOTYKTU and had PASI 90 response at Week 24, the PASI 90 response at Week 52 was 74% (103/140).

In PSO-2, to evaluate maintenance and durability of response, subjects who were originally randomized to SOTYKTU and were PASI 75 responders at Week 24, were re-randomized to either continue treatment on SOTYKTU or be withdrawn from therapy (i.e., receive placebo).

For subjects who were re-randomized and also had a sPGA score of 0 or 1 at Week 24, 70% (83/118) of subjects who continued on SOTYKTU maintained this response (sPGA 0 or 1) at Week 52 compared to 24% (28/119) of subjects who were re-randomized to placebo. In addition, at Week 52, 80% (119/148) of subjects who continued on SOTYKTU maintained PASI 75 compared to 31% (47/150) of subjects who were withdrawn from SOTYKTU.

For sPGA 0 or 1 responders at Week 24 who were re-randomized to treatment withdrawal (i.e., placebo), the median time to loss of sPGA score of 0 or 1 was approximately 8 weeks. For PASI 75 responders at Week 24 who were re-randomized to treatment withdrawal (i.e., placebo), the median time to loss of PASI 75 was approximately 12 weeks.

Patient Reported Outcomes

A greater proportion of subjects treated with SOTYKTU compared to placebo achieved Psoriasis Symptoms and Signs Diary (PSSD) symptom score of 0 (absence of itch, pain, burning, stinging, and skin tightness) at Week 16 (8% in SOTYKTU vs. 1% in placebo) in both trials.

16 HOW SUPPLIED/STORAGE AND HANDLING

16.1 How Supplied

SOTYKTU™ (deucravacitinib) tablets are available as listed in the table below:

Tablet Strength | Tablet Color/Shape | Tablet Markings | Package Size | NDC Code
6 mg | Pink, round, biconvex, film-coated tablet | Laser printed with “BMS 895” and “6 mg” on one side | Bottles of 30 with child-resistant closure | 0003-0895-11

16.2 Storage and Handling

Store SOTYKTU tablets at 20° to 25°C (68° to 77°F); excursions permitted between 15° and 30°C (59° and 86°F) [see USP Controlled Room Temperature].

17 PATIENT COUNSELING INFORMATION

Advise the patient to read the FDA-approved patient labeling (Medication Guide) before starting SOTYKTU therapy and each time the prescription is renewed, as there may be new information they need to know. Advise patients of the potential benefits and risks of SOTYKTU.

Hypersensitivity Reactions

Advise patients to discontinue SOTYKTU and seek immediate medical attention if they experience any symptoms of serious hypersensitivity reactions [see Warnings and Precautions (5.1)].

Infections

Inform patients that SOTYKTU may lower the ability of their immune system to fight infections and to contact their healthcare provider immediately if they develop any signs or symptoms of infection [see Warnings and Precautions (5.2)].

Inform patients that herpes infections, including serious, may occur with use of SOTYKTU [see Warnings and Precautions (5.2)].

Malignancies including Lymphomas

Inform patients that SOTYKTU may increase their risk of developing malignancies including lymphomas. Instruct patients to inform their healthcare provider if they have ever had any type of cancer [see Warnings and Precautions (5.4)].

Rhabdomyolysis

Inform patients that SOTYKTU may increase their risk of developing rhabdomyolysis. Instruct patients to immediately inform their healthcare provider if they develop unexplained muscle pain, tenderness or weakness, particularly if accompanied by malaise or fever [see Warnings and Precautions (5.5)].

Laboratory Abnormalities

Inform patients that SOTYKTU may affect certain lab tests, and that blood tests may be required before and during SOTYKTU treatment [see Warnings and Precautions (5.6)].

Immunizations

Advise patients that vaccination with live vaccines is not recommended during SOTYKTU treatment. Medications that interact with the immune system may increase the risk of infection following administration of live vaccines. Instruct patients to inform the healthcare practitioner that they are taking SOTYKTU prior to a potential vaccination [see Warnings and Precautions (5.7)].

Pregnancy

Advise patients to report their pregnancy to Bristol-Myers Squibb Company at 1-800-721-5072 [see Use in Specific Populations (8.1)].

MEDICATION GUIDE

SOTYKTU™ (soh-tik-too)

(deucravacitinib)

tablets

What is the most important information I should know about SOTYKTU?

SOTYKTU may cause serious side effects, including:

- Serious allergic reactions. Stop taking SOTYKTU and get emergency medical help right away if you develop any of the following symptoms of a serious allergic reaction:

- feel faint
- swelling of your face, eyelids, lips, mouth, tongue, or throat

- trouble breathing or throat tightness
- chest tightness
- skin rash, hives

- Infections. SOTYKTU is a medicine that affects your immune system. SOTYKTU can lower the ability of your immune system to fight infections and can increase your risk of infections. Some people have had serious infections while taking SOTYKTU, such as infections of the lungs, including pneumonia and tuberculosis (TB), and COVID-19.
  - Your healthcare provider should check you for infections and TB before starting treatment with SOTYKTU.
  - Your healthcare provider may treat you for TB before you begin treatment with SOTYKTU if you have a history of TB or have active TB.
  - Your healthcare provider should watch you closely for signs and symptoms of TB during treatment with SOTYKTU.
  - If you get a serious infection, your healthcare provider may tell you to stop taking SOTYKTU until your infection is controlled.
SOTYKTU should not be used in people with an active, serious infection, including localized infections. You should not start taking SOTYKTU if you have any kind of infection unless your healthcare provider tells you it is okay.
You may be at a higher risk of developing shingles (herpes zoster).
Before starting SOTYKTU, tell your healthcare provider if you:
  - are being treated for an infection
  - have had an infection that does not go away or keeps coming back
  - have TB or have been in close contact with someone with TB
  - have or have had hepatitis B or C
  - think you have an infection or have symptoms of an infection such as:

- fever, sweats, or chills
- muscle aches
- weight loss
- cough
- shortness of breath
- blood in your phlegm (mucus)

- warm, red, or painful skin or sores on your body different from your psoriasis
- diarrhea or stomach pain
- burning when you urinate or urinating more often than normal
- feeling very tired

After you start taking SOTYKTU, call your healthcare provider right away if you have an infection or have symptoms of an infection.
SOTYKTU can make you more likely to get infections or make any infections you have worse.
3. Cancer. Certain kinds of cancer including lymphoma have been reported in people taking SOTYKTU.
  - Tell your healthcare provider if you have ever had any type of cancer.
4. Muscle problems (rhabdomyolysis). SOTYKTU can cause muscle problems that can be severe. Treatment with SOTYKTU may increase the level of an enzyme in your blood called creatine phosphokinase (CPK) and can be a sign of muscle damage. Increased CPK is common in people taking SOTYKTU. Your healthcare provider may tell you to stop taking SOTYKTU if the amount of CPK in your blood gets too high or if you have signs and symptoms of severe muscle problems. Tell your healthcare provider right away if you have any of these signs or symptoms of severe muscle problems:

- unexplained muscle pain, tenderness, or weakness
- feeling very tired

- fever
- dark-colored urine

See “What are the possible side effects of SOTYKTU?” for more information about side effects.

What is SOTYKTU?

SOTYKTU is a prescription medicine used to treat adults with moderate to severe plaque psoriasis who may benefit from taking injections or pills (systemic therapy) or treatment using ultraviolet or UV light (phototherapy).

It is not known if SOTYKTU is safe and effective in children under 18 years of age.

Do not take SOTYKTU if you are allergic to deucravacitinib or any of the ingredients in SOTYKTU. See the end of this Medication Guide for a complete list of ingredients in SOTYKTU.

Before taking SOTYKTU, tell your healthcare provider about all of your medical conditions, including if you:

- See “What is the most important information I should know about SOTYKTU?”
- have liver problems or kidney problems
- have high levels of fat in your blood (triglycerides)
- have recently received or are scheduled to receive an immunization (vaccine). You should avoid receiving live vaccines during treatment with SOTYKTU.
- are pregnant or plan to become pregnant. It is not known if SOTYKTU can harm your unborn baby.
  - Report pregnancies to the Bristol-Myers Squibb Company’s Adverse Event reporting line at 1-800-721-5072.
- are breastfeeding or plan to breastfeed. It is not known if SOTYKTU passes into your breast milk.

Tell your healthcare provider about all the medicines you take, including prescription medicines, over-the-counter medicines, vitamins, and herbal supplements. Keep a list of them to show your healthcare provider and pharmacist when you get a new medicine.

How should I take SOTYKTU?

- Take SOTYKTU exactly as your healthcare provider tells you to take it.
- Take SOTYKTU 1 time every day.
- Take SOTYKTU with or without food.
- Do not crush, cut, or chew the SOTYKTU tablets.

What are the possible side effects of SOTYKTU?

SOTYKTU may cause serious side effects, including:

- See “What is the most important information I should know about SOTYKTU?”
- Changes in certain laboratory test results. Changes in laboratory tests have happened in some people taking SOTYKTU. Your healthcare provider may do blood tests before you start taking SOTYKTU and during treatment with SOTYKTU to check for the following:
  - Increased triglycerides. Triglycerides are a type of fat found in your blood. Too much fat in your blood can cause problems with your heart.
  - Increased liver enzymes. Liver enzymes are found in your blood and help to tell if your liver is functioning normally. If your liver enzymes increase too much, your healthcare provider may need to do additional tests on your liver and may tell you to stop taking SOTYKTU if they think that SOTYKTU is harming your liver.
- Potential risks from Janus kinase (JAK) inhibition. SOTYKTU is a tyrosine kinase 2 (TYK2) inhibitor. TYK2 is in the JAK family. It is not known whether taking SOTYKTU has the same risks as taking JAK inhibitors. Increased risk of death (all causes) has happened in people who were 50 years of age and older with at least 1 heart disease (cardiovascular) risk factor who were taking a JAK inhibitor used to treat rheumatoid arthritis (RA) compared to people taking another medicine in a class of medicines called TNF blockers. SOTYKTU is not for use in people with RA.

The most common side effects of SOTYKTU include:

- common cold, sore throat, and sinus infection (upper respiratory infections)
- cold sores (herpes simplex)

- sores on inner lips, gums, tongue, or roof of the mouth (canker sores)
- inflamed hair pores (folliculitis)
- acne

These are not all of the possible side effects of SOTYKTU.

Call your doctor for medical advice about side effects. You may report side effects to FDA at 1-800-FDA-1088.

How should I store SOTYKTU?

Store SOTYKTU at room temperature between 68°F to 77°F (20°C to 25°C).

Keep SOTYKTU and all medicines out of the reach of children.

General information about the safe and effective use of SOTYKTU.

Medicines are sometimes prescribed for purposes other than those listed in a Medication Guide. Do not use SOTYKTU for a condition for which it was not prescribed. Do not give SOTYKTU to other people, even if they have the same symptoms that you have. It may harm them. You can ask your pharmacist or healthcare provider for information about SOTYKTU that is written for health professionals.

What are the ingredients in SOTYKTU?

Active ingredient: deucravacitinib.

Inactive ingredients: anhydrous lactose, croscarmellose sodium, hypromellose acetate succinate, magnesium stearate, microcrystalline cellulose and silicon dioxide. In addition, the film coating Opadry® II Pink contains the following inactive ingredients: polyvinyl alcohol, titanium dioxide, polyethylene glycol, talc, iron oxide red and yellow.

Distributed by:

Bristol-Myers Squibb Company

Princeton, New Jersey 08543 USA

For more product information about SOTYKTU, go to website (www.sotyktu.com) or call SOTYKTU 360 SUPPORT at 1.888.SOTYKTU (768.9588).

This Medication Guide has been approved by the U.S. Food and Drug Administration.

Issued: 9/2022

PACKAGE/LABEL PRINCIPAL DISPLAY PANEL

NDC 0003-0895-11

30 Tablets

SOTYKTUTM

(deucravacitinib)

tablets

6 mg

Rx only

Bristol Myers Squibb